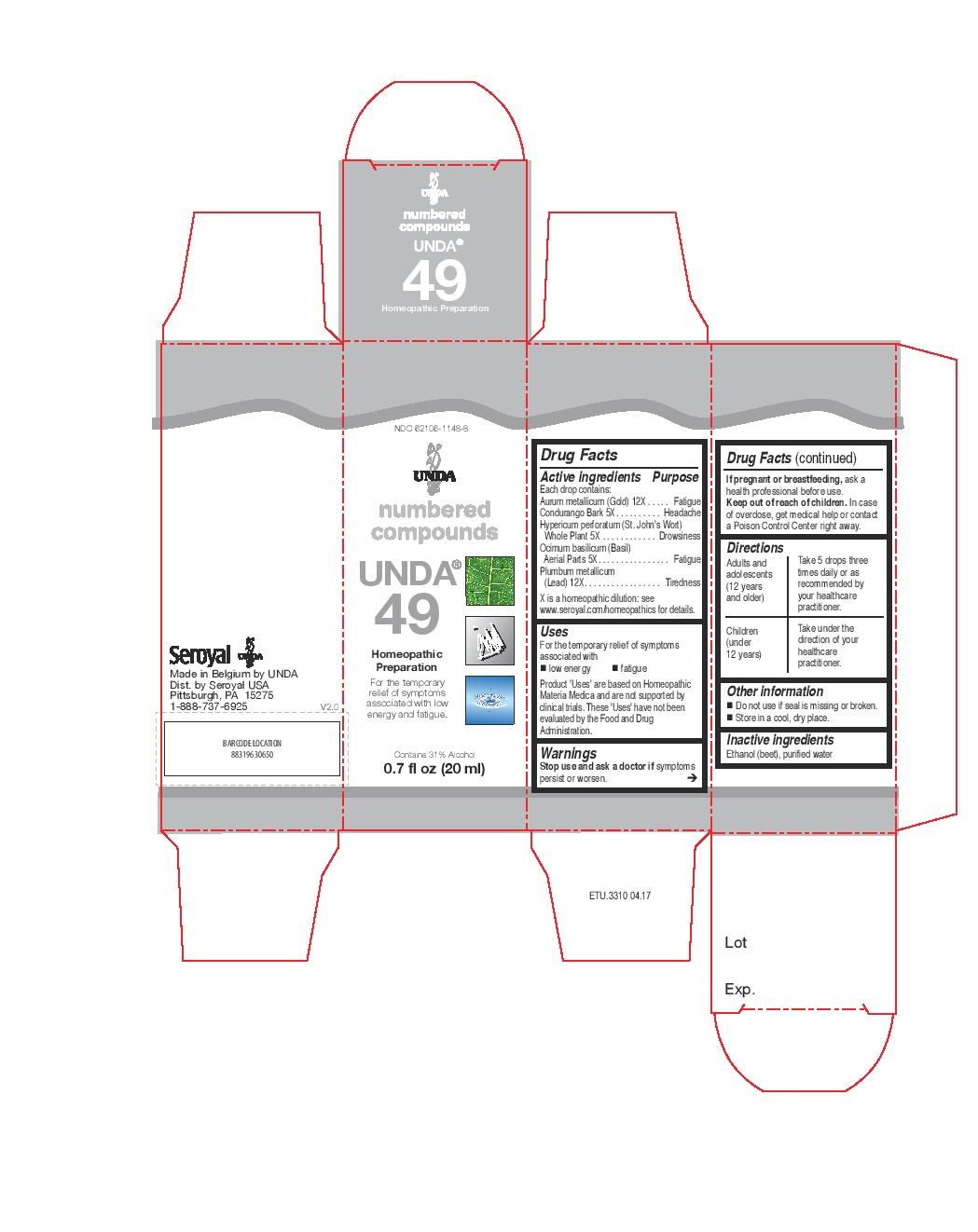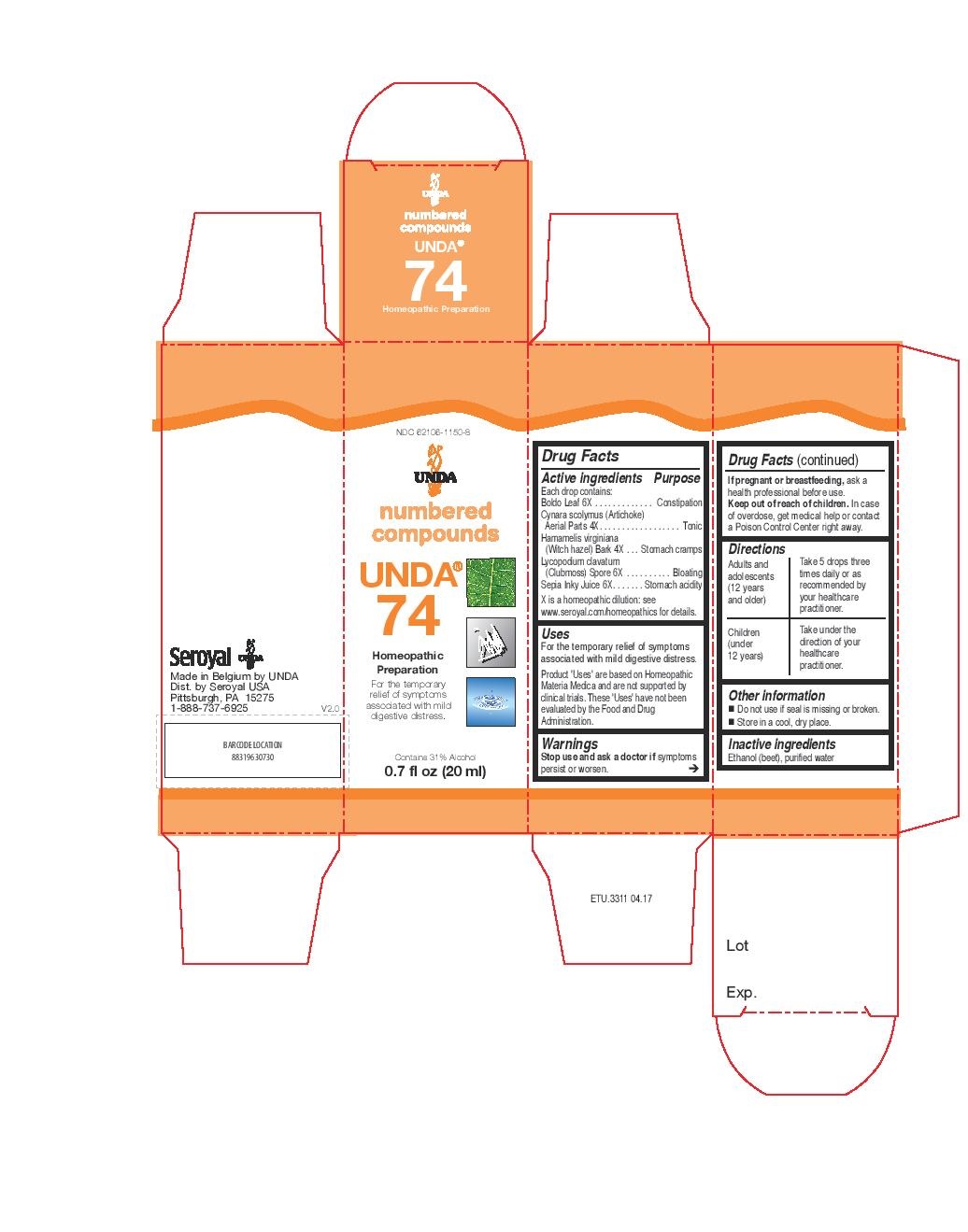 DRUG LABEL: UNDA 49
NDC: 62106-1148 | Form: LIQUID
Manufacturer: Seroyal USA
Category: homeopathic | Type: HUMAN OTC DRUG LABEL
Date: 20221109

ACTIVE INGREDIENTS: GOLD 12 [hp_X]/20 mL; MARSDENIA CONDURANGO BARK 5 [hp_X]/20 mL; BASIL 5 [hp_X]/20 mL; LEAD 12 [hp_X]/20 mL; HYPERICUM PERFORATUM 5 [hp_X]/20 mL
INACTIVE INGREDIENTS: ALCOHOL; WATER

UNDA 49 and 74

Active ingredients

Each drop contains:
Aurum metallicum (Gold) 12X
Condurango Bark 5X
Hypericum perforatum (St. John's Wort) Whole Plant 5X
Ocimum basilicum (Basil) Aerial Parts 5X
Plumbum metallicum (Lead) 12X

Uses
For the temporary relief of symptoms associated with low energy and fatigue

Warnings
Stop use and ask a doctor if symptoms persist or worsen.
If pregnant or breastfeeding, ask a health professional before use.
Keep out of reach of children.
In case of overdose, get medical help or contact a Poison Control Center right away.

Stop use and ask a doctor if symptoms persist or worsen.

PREGNANCY OR BREAST FEEDING

If pregnant or breastfeeding, ask a health professional before use.

Keep out of reach of children.

OVERDOSAGE

In case of overdose, get medical help or contact a Poison Control Center right away.

Inactive ingredients
Ethanol (beet), purified water

Other information
Do not use if seal is missing or broken.
Store in a cool, dry place.

Directions
Adults and adolescents (12 years and older): Take 5 drops three times daily or as
recommended by your healthcare practitioner.
Children (under 12 years): Take under the direction of your
healthcare practitioner.

Uses
For the temporary relief of symptoms associated with low energy and fatigue

Directions
Adults and adolescents (12 years and older): Take 5 drops three times daily or as
recommended by your healthcare practitioner.
Children (under 12 years): Take under the direction of your
healthcare practitioner.

Active ingredients

Each drop contains:

Boldo Leaf 6X
Cynara scolymus (Artichoke) Aerial Parts 4X
Hamamelis virginiana (Witch hazel) Bark 4X
Lycopodium clavatum (Clubmoss) Spore 6X
Sepia Inky Juice 6X

Uses
For the temporary relief of symptoms associated with mild digestive distress.

Warnings
Stop use and ask a doctor if symptoms persist or worsen.
If pregnant or breastfeeding, ask a health professional before use.
Keep out of reach of children.
In case of overdose, get medical help or contact a Poison Control Center right away.

Stop use and ask a doctor if symptoms persist or worsen.

PREGNANCY OR BREAST FEEDING

If pregnant or breastfeeding, ask a health professional before use.

Keep out of reach of children.

OVERDOSAGE

In case of overdose, get medical help or contact a Poison Control Center right away.

Inactive ingredients
Ethanol (beet), purified water

Other information
Do not use if seal is missing or broken.
Store in a cool, dry place.

Directions
Adults and adolescents (12 years and older): Take 5 drops three times daily or as
recommended by your healthcare practitioner.
Children (under 12 years): Take under the direction of your
healthcare practitioner.

Uses
For the temporary relief of symptoms associated with mild digestive distress.

Directions
Adults and adolescents (12 years and older): Take 5 drops three times daily or as
recommended by your healthcare practitioner.
Children (under 12 years): Take under the direction of your
healthcare practitioner.

PACKAGE LABEL

NDC 62106-1148-8

UNDA
numbered compounds
UNDA 49
Homeopathic Preparation

For the temporary relief of symptoms
associated with low energy and fatigue.
Contains 31% Alcohol
0.7 fl oz (20 ml)

PACKAGE LABEL

NDC 62106-1150-8

UNDA
numbered compounds
UNDA 74
Homeopathic Preparation

For the temporary relief of symptoms
associated with mild digestive distress.
Contains 31% Alcohol
0.7 fl oz (20 ml)